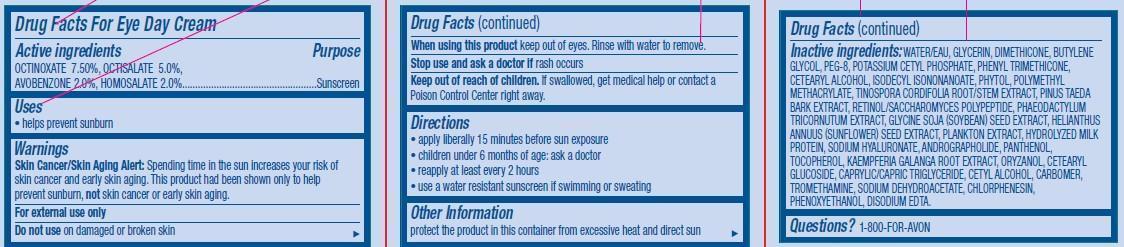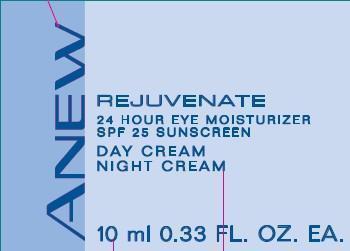 DRUG LABEL: Anew Rejuvenate
NDC: 10096-0149 | Form: CREAM
Manufacturer: Avon Products, Inc
Category: otc | Type: HUMAN OTC DRUG LABEL
Date: 20130208

ACTIVE INGREDIENTS: OCTINOXATE 75 mg/1 mL; OCTISALATE 50 mg/1 mL; AVOBENZONE 20 mg/1 mL; HOMOSALATE 20 mg/1 mL

Active ingredients
OCTINOXATE 7.50%, OCTISALATE 5.0%,
AVOBENZONE 2.0%, HOMOSALATE 2.0%..............................

Purpose
................................Sunscreen

Uses

- helps prevent sunburn

Warnings
Skin Cancer/Skin Aging Alert: Spending time in the sun increases your risk of skin cancer and early skin aging. This product had been shown only to help prevent sunburn, not skin cancer or early skin aging.
For external use only

Do not use on damaged or broken skin

When using this product keep out of eyes. Rinse with water to remove.

Stop use and ask a doctor if rash occurs

Keep out of reach of children. If swallowed, get medical help or contact a Poison Control Center right away.

Directions

- apply liberally 15 minutes before sun exposure
- children under 6 months of age: ask a doctor
- reapply at least every 2 hours
- use a water resistant sunscreen if swimming or sweating

Other Information
protect the product in this container from excessive heat and direct sun

INACTIVE INGREDIENT

Inactive ingredients:WATER/EAU, GLYCERIN, DIMETHICONE, BUTYLENE GLYCOL, PEG-8, POTASSIUM CETYL PHOSPHATE, PHENYL TRIMETHICONE, CETEARYL ALCOHOL, ISODECYL ISONONANOATE, PHYTOL, POLYMETHYL METHACRYLATE, TINOSPORA CORDIFOLIA ROOT/STEM EXTRACT, PINUS TAEDA BARK EXTRACT, RETINOL/SACCHAROMYCES POLYPEPTIDE, PHAEODACTYLUM TRICORNUTUM EXTRACT, GLYCINE SOJA (SOYBEAN) SEED EXTRACT, HELIANTHUS ANNUUS (SUNFLOWER) SEED EXTRACT, PLANKTON EXTRACT, HYDROLYZED MILK
PROTEIN, SODIUM HYALURONATE, ANDROGRAPHOLIDE, PANTHENOL, TOCOPHEROL, KAEMPFERIA GALANGA ROOT EXTRACT, ORYZANOL, CETEARYL GLUCOSIDE, CAPRYLIC/CAPRIC TRIGLYCERIDE, CETYL ALCOHOL, CARBOMER, TROMETHAMINE, SODIUM DEHYDROACETATE, CHLORPHENESIN, PHENOXYETHANOL, DISODIUM EDTA.

Questions?1-800-FOR-AVON